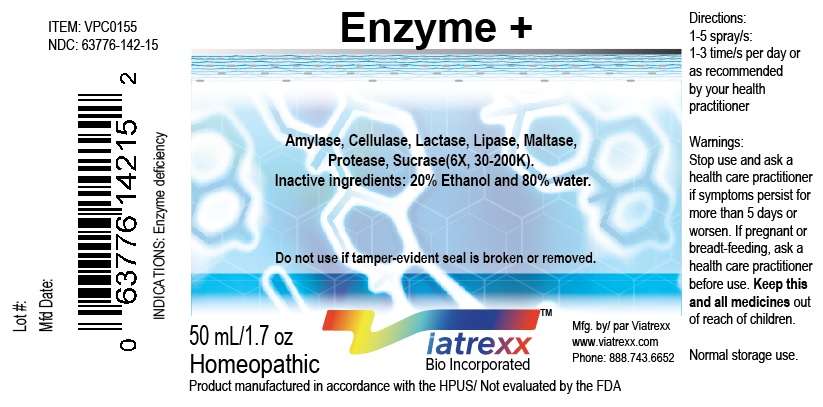 DRUG LABEL: Viatrexx-Enzyme Plus
NDC: 63776-142 | Form: SPRAY
Manufacturer: VIATREXX BIO INCORPORATED
Category: homeopathic | Type: HUMAN OTC DRUG LABEL
Date: 20190319

ACTIVE INGREDIENTS: Pancreatic Alpha-Amylase 30 [kp_C]/1 mL; Cellulase (Trichoderma Longibrachiatum) 30 [kp_C]/1 mL; Lactase 30 [kp_C]/1 mL; Pancreatic Triacylglycerol Lipase 30 [kp_C]/1 mL; Lysosomal Alpha-Glucosidase 30 [kp_C]/1 mL; Pancrelipase Protease 30 [kp_C]/1 mL; Sacrosidase 30 [kp_C]/1 mL
INACTIVE INGREDIENTS: Water; Alcohol

Enzyme +

Active Ingredients

Amylase (6X, 30K & 200K), Cellulase (6X, 30K & 200K), Lactase (6X, 30K & 200K), Lipase (6X, 30K & 200K), Maltase (6X, 30K & 200K), Protease (6X, 30K & 200K), Sucrase (6X, 30K & 200K)

Purpose

Amylase
Cellulase
Lactase
Lipase
Maltase
Protease
Sucrase

Enzyme for Starches
Enzyme for Cellulose
Enzyme for Lactose and dairy
Enzyme for Fats
Enzyme for Maltose
Enzyme for Proteins
Enzyme for Sugars

Description

Viatrexx-Enzyme + is a homeopathic product composed of physiological (low dose and low low dose) natural micro nutrients. These micro particles are designed to nourish the system.

Uses

To support healthy digestion.

Warnings

Stop use and ask a health care practitioner if symptoms persist for more than five days or worsen. If pregnant or breastfeeding, ask a health care practitioner before use.

Dosage

1-3 spray(s); 1-3 time(s) per day or as recommended by your health care practitioner.

Inactive Ingredients

20% Alcohol and 80% Water

Other Information

Product availability

Product may be acquired in 0.5, 30, 50, 100, 250 mL bottles.

References upon request

To report SUSPECTED ADVERSE REACTIONS, contact the FDA at 1-800-FDA-1088 or www.fda.gov/medwatch

Distributed by
Viatrexx Bio Incorporated
Newark, DE, USA, 19713

Manufactured by
8046255 Canada Inc
Beloeil, Qc, J3G 6S3
Date of last revision March 2019

For Questions and comments
Info@Viatrexx.com
www.Viatrexx.com

PACKAGE LABEL.PRINCIPAL DISPLAY PANEL

NDC: 63776-142-11
Item: VPC0045
Viatrexx Bio Incorporated
Viatrexx- Enzyme +
Box of 1 X 0.5 mL ampule
For Oral and Topical Use
Expiry date: Lot #:
Manufactured for:
Viatrexx Bio Incorporated Newark, DE, USA, 19713
www.Viatrexx.com
Ingredients, homeopathic
See insert or www.viatrexx.com
Inactives: Alcohol 20%, Water 80%

NDC: 63776-142-14
Item: VPC0045
Viatrexx Bio Incorporated
Viatrexx-Enzyme +
Box of 1 X 30 mL spray bottle
For Oral and Topical Use
Expiry date: Lot #:
Manufactured for:
Viatrexx Bio Incorporated Newark, DE, USA, 19713
www.Viatrexx.com
Ingredients, homeopathic
See insert or www.viatrexx.com
Inactives: Alcohol 20%, Water 80%

NDC: 63776-142-15
Item: VPC0045
Viatrexx Bio Incorporated
Viatrexx-Enzyme +
Box of 1 X 50 mL spray bottle
For Oral and Topical Use
Expiry date: Lot #:
Manufactured for:
Viatrexx Bio Incorporated Newark, DE, USA, 19713
www.Viatrexx.com
Ingredients, homeopathic
See insert or www.viatrexx.com
Inactives: Alcohol 20%, Water 80%

NDC: 63776-142-16
Item: VPC0045
Viatrexx Bio Incorporated
Viatrexx-Enzyme +
Box of 1 X 100 mL bottle
For Oral and Topical Use
Expiry date: Lot #:
Manufactured for:
Viatrexx Bio Incorporated Newark, DE, USA, 19713
www.Viatrexx.com
Ingredients, homeopathic
See insert or www.viatrexx.com
Inactives: Alcohol 20%, Water 80%

NDC: 63776-142-17
Item: VPC0045
Viatrexx Bio Incorporated
Viatrexx-Enzyme +
Box of 1 X 250 mL bottle
For Oral and Topical Use
Expiry date: Lot #:
Manufactured for:
Viatrexx Bio Incorporated Newark, DE, USA, 19713
www.Viatrexx.com
Ingredients, homeopathic
See insert or www.viatrexx.com
Inactives: Alcohol 20%, Water 80%